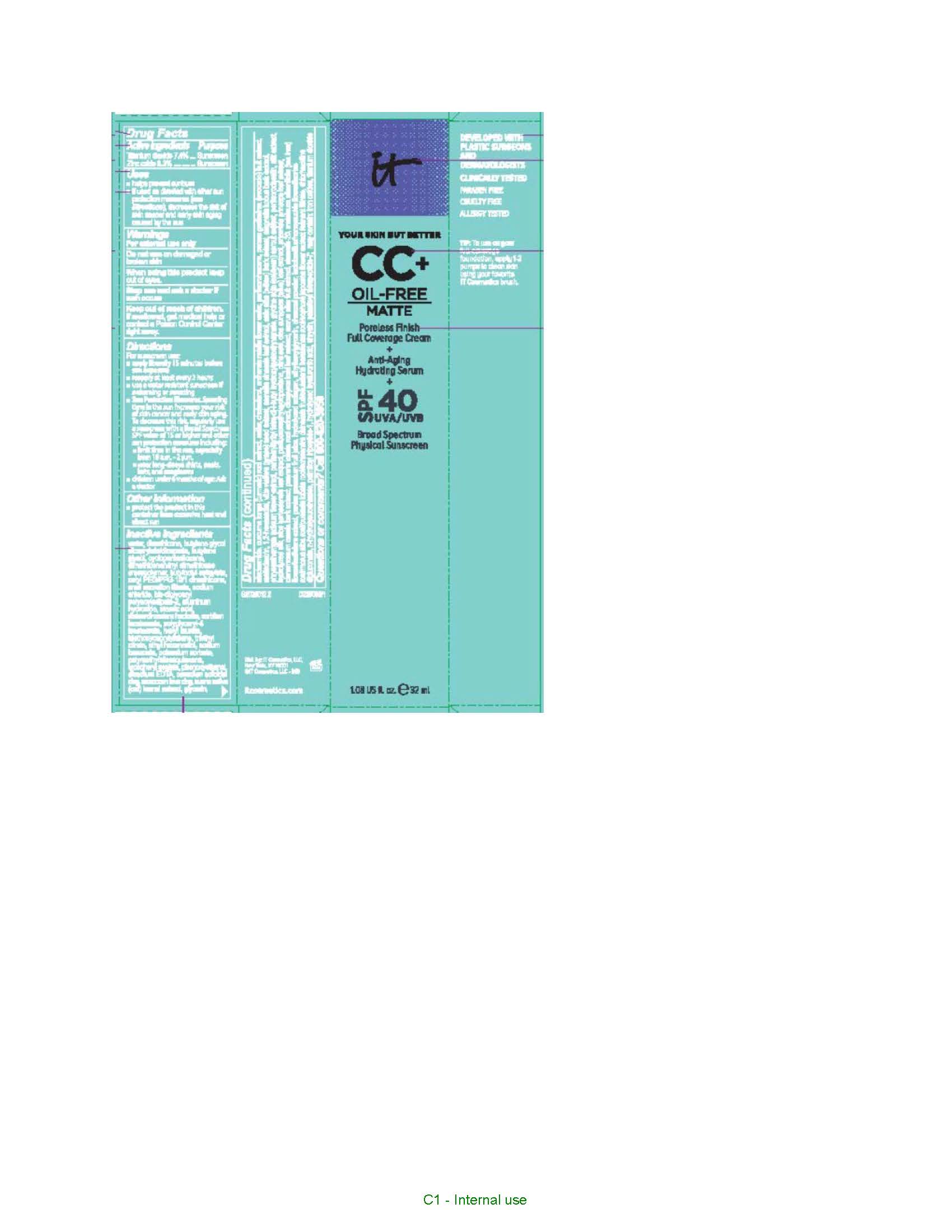 DRUG LABEL: it cosmetics Your Skin But Better CC Plus Oil Free Matte Poreless Finish Full Coverage Broad Spectrum SPF 40 Sunscreen All Shades
NDC: 69259-2522 | Form: CREAM
Manufacturer: IT COSMETICS, LLC
Category: otc | Type: HUMAN OTC DRUG LABEL
Date: 20250325

ACTIVE INGREDIENTS: TITANIUM DIOXIDE 74 mg/1 mL; ZINC OXIDE 63 mg/1 mL
INACTIVE INGREDIENTS: WATER; DIMETHICONE; BUTYLENE GLYCOL DICAPRYLATE/DICAPRATE; BUTYLENE GLYCOL; CYCLOMETHICONE 5; DIMETHICONE/VINYL DIMETHICONE CROSSPOLYMER (HARD PARTICLE); BUTYLOCTYL SALICYLATE; CETYL PEG/PPG-10/1 DIMETHICONE (HLB 1.5); SODIUM CHLORIDE; BIS-DIGLYCERYL POLYACYLADIPATE-2; ALUMINUM HYDROXIDE; STEARIC ACID; DISTEARDIMONIUM HECTORITE; SORBITAN ISOSTEARATE; POLYGLYCERYL-4 ISOSTEARATE; HEXYL LAURATE; TRIETHOXYCAPRYLYLSILANE; TRIETHYL CITRATE; ETHOHEXADIOL; SODIUM BENZOATE; POTASSIUM SORBATE; POLYMETHYLSILSESQUIOXANE (11 MICRONS); .ALPHA.-TOCOPHEROL ACETATE, D-; PHENOXYETHANOL; EDETATE DISODIUM; GLYCERIN; NIACINAMIDE; SULFUR; CHOLESTEROL; PERFLEXANE; MALTODEXTRIN; 1,2-HEXANEDIOL; VITIS VINIFERA ANTHOCYANINS; GREEN TEA LEAF; PENTAERYTHRITOL TETRAKIS(3-(3,5-DI-TERT-BUTYL-4-HYDROXYPHENYL)PROPIONATE); PERFLUNAFENE; ALOE VERA LEAF; PERFLUOROMETHYLCYCLOPENTANE; CITRIC ACID MONOHYDRATE; CHINESE CINNAMON; STEARETH-20; POMEGRANATE JUICE; ETHYLHEXYLGLYCERIN; ACTIVATED CHARCOAL; CHLORHEXIDINE; N-HYDROXYSUCCINIMIDE; PALMITOYL TRIPEPTIDE-1; CHRYSIN; PALMITOYL TETRAPEPTIDE-7; FERRIC OXIDE RED

Active ingredients

Titanium dioxide 7.4%

Zinc oxide 6.3%%

Purpose

Sunscreen

Uses

- helps prevent sunburn
- if used as directed with other sun protection measures (see Directions), decreases the risk of skin cancer and early skin aging caused by the sun

Warnings

For external use only

Do not use

on damaged or broken skin

When using this product

keep out of eyes. Rinse with water to remove.

Stop use and ask a doctor if

rash occurs

Keep out of reach of children.

If swallowed, get medical help or contact a Poison Control Center right away.

Directions

For sunscreen use:
● apply liberally 15 minutes before sun exposure
● reapply at least every 2 hours
● use a water resistant sunscreen if swimming or sweating
● Sun Protection Measures. Spending time in the sun increases your risk of skin cancer and early skin aging. To decrease this risk, regularly use a sunscreen with a Broad Spectrum SPF value of 15 or higher and other sun protection measures including:
● limit time in the sun, especially from 10 a.m. – 2 p.m.
● wear long-sleeved shirts, pants, hats, and sunglasses
● children under 6 months of age: Ask a doctor

Other information

protect the product in this container from excessive heat and direct sun

Inactive ingredients

water, dimethicone, butylene glycol dicaprylate/dicaprate, butylene glycol, cyclopentasiloxane, dimethicone/vinyl dimethicone crosspolymer, butyloctyl salicylate, cetyl PEG/PPGg-10/1 dimethicone, snail secretion filtrate, sodium chloride, bis-diglyceryl polyacyladipate-2, aluminum hydroxide, stearic acid, disteardimonium hectorite, sorbitan isostearate, polyglyceryl-4 isostearate, hexyl laurate, triethoxycaprylylsilane, triethyl citrate, ethyl hexanediol, sodium benzoate, potassium sorbate, polymethylsilsesquioxane, tocopheryl acetate, phenoxyethanol, disodium EDTA, canadian colloidal clay, moroccan lava clay, avena sativa (oat) kernel extract, glycerin, niacinamide, curcuma longa (turmeric) root extract, sulfur, cholesterol, anthemis nobilis flower water, perfluorohexane, persea gratissima (avocado) fruit extract, maltodextrin, 1,2-hexanediol, vitis vinifera (grape) seed extract, camellia sinensis leaf extract, salix alba (willow) bark extract, magnolia kobus bark extract, chrysanthemum indicum flower extract, pentaerythrityl tetra-di-t-butyl hydroxyhydrocinnamate, glycine soja (soybean) sprout extract, perfluorodecalin, silk extract, hydrolyzed silk, aloe barbadensis leaf extract, perfluoromethylcyclopentane, citric acid, olea europaea (olive) leaf extract, artemisia princeps leaf extract, cinnamomum cassia bark extract, pueraria lobata root extract, diospyros kaki leaf extract, morus alba fruit extract, steareth-20, melaleuca alternifolia (tea tree) flower/leaf/stem extract, punica granatum fruit juice, hydrolyzed collagen, ethylhexylglycerin, charcoal powder, lactobacillus/honeysuckle flower/licorice root/morus alba root/pueraria lobata root/schisandra chinensis fruit/scutellaria baicalensis root/sophora japonica flower extract ferment filtrate, chlorhexidine digluconate, n-hydroxysuccinimide, palmitoyl tripeptide-1, hydrolyzed hyaluronic acid, chrysin, palmitoyl tetrapeptide-7; may contain: iron oxides, titanium dioxide

Questions or comments?

Call 800-620-3950